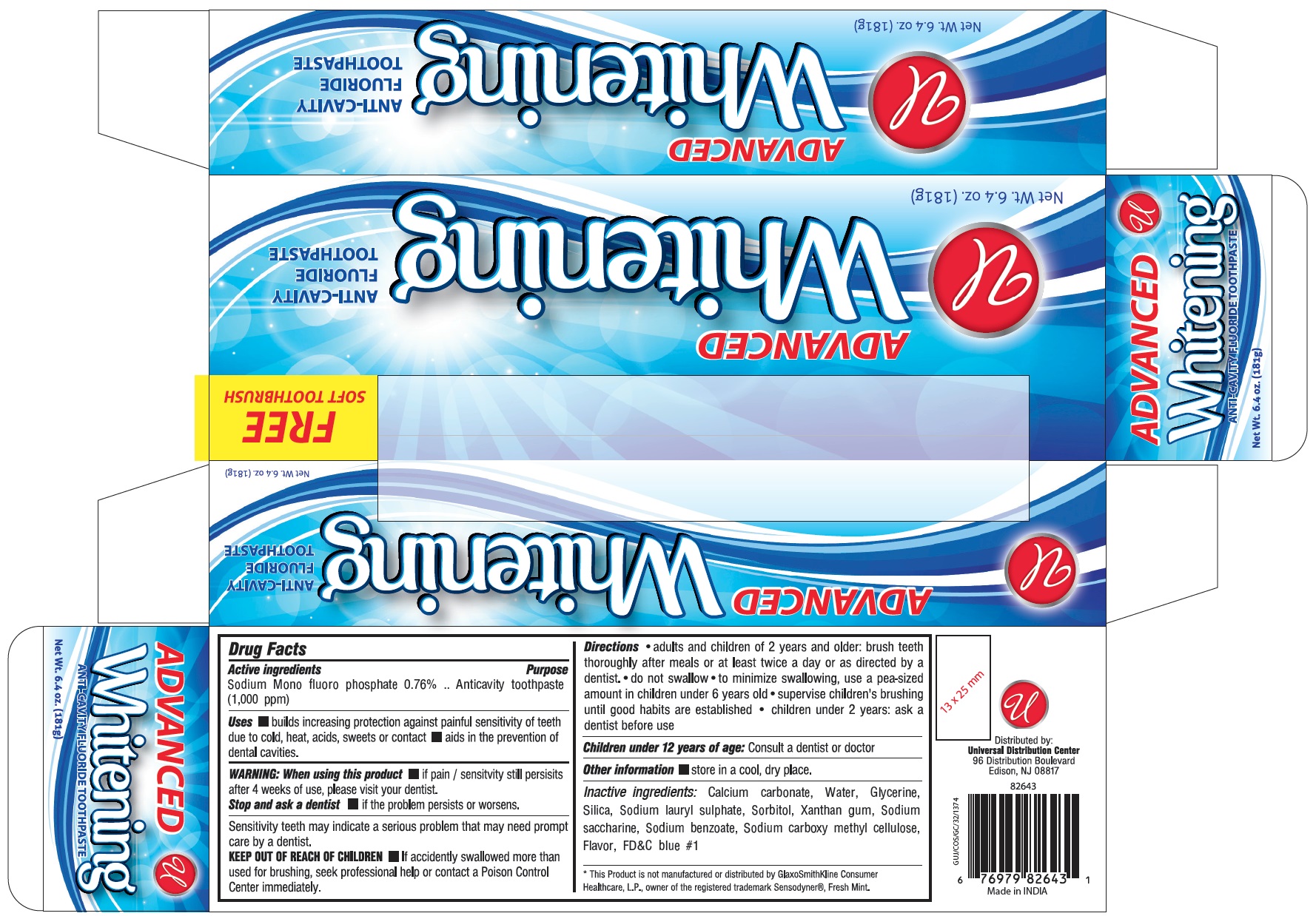 DRUG LABEL: ADVANCED WHITENING ANTI CAVITY FLUORIDE
NDC: 52000-108 | Form: PASTE
Manufacturer: Universal Distribution Center LLC
Category: otc | Type: HUMAN OTC DRUG LABEL
Date: 20231116

ACTIVE INGREDIENTS: SODIUM MONOFLUOROPHOSPHATE 0.76 g/100 g
INACTIVE INGREDIENTS: CALCIUM CARBONATE; WATER; GLYCERIN; SILICON DIOXIDE; SODIUM LAURYL SULFATE; SORBITOL; XANTHAN GUM; SACCHARIN SODIUM; SODIUM BENZOATE; CARBOXYMETHYLCELLULOSE SODIUM, UNSPECIFIED FORM; FD&C BLUE NO. 1

UNIVERSAL ADVANCED WHITENING ANTI-CAVITY FLUORIDE TOOTHPASTE

Active Ingredient

Sodium Monofluorophosphate 0.76%

(1000 ppm)

Purpose

Anticavity toothpaste

Uses

- builds increasing protection against painful sensitivity of teeth due to cold, heat, acids, sweets or contact.
- aids in the prevention of dental cavities.

Warning

When using this product

- if pain\ sensitivity still persists after 4 weeks of use, please visit your dentist.

Stop and ask a dentist

- if the problem persists or worsens.

Sensitivity teeth may indicate a serious problem that may need prompt care by a dentist.

Keep out of reach of children

- If accidentally swallowed more than used for brushing, seek professional help or contact a Poison Control Center immediately.

Directions

- adults and children of 2 years and older: brush teeth thoroughly after meals or at least twice a day, or as directed by a dentist.
- do not swallow.
- to minimize swallowing, use a pea-sized amount in children under 6 years old.
- supervise children's brushing until good habits are established.
- children under 2 years: ask a dentist before use.

Children under 12 years of age: Consult a dentist or doctor

Other information

- store in a cool, dry place.

Inactive Ingredients

Calcium carbonate, Water, Glycerine, Silica, Sodium Lauryl sulphate, Sorbitol, Xanthan gum, Sodium saccharine, Sodium benzoate, Sodium carboxy methyl cellulose, Flavor and FD&C blue #1

PACKAGE LABEL

PRINCIPAL DISPLAY PANEL

ADVANCED WHITENING ANTI-CAVITY FLUORIDE TOOTHPASTE